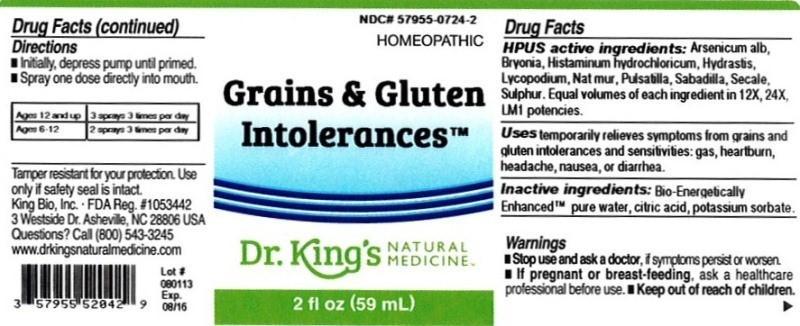 DRUG LABEL: Grains and Gluten Intolerances
NDC: 57955-0724 | Form: LIQUID
Manufacturer: King Bio Inc.
Category: homeopathic | Type: HUMAN OTC DRUG LABEL
Date: 20131119

ACTIVE INGREDIENTS: ARSENIC TRIOXIDE 12 [hp_X]/59 mL; BRYONIA ALBA ROOT 12 [hp_X]/59 mL; HISTAMINE DIHYDROCHLORIDE 12 [hp_X]/59 mL; GOLDENSEAL 12 [hp_X]/59 mL; LYCOPODIUM CLAVATUM SPORE 12 [hp_X]/59 mL; SODIUM CHLORIDE 12 [hp_X]/59 mL; PULSATILLA VULGARIS 12 [hp_X]/59 mL; SCHOENOCAULON OFFICINALE SEED 12 [hp_X]/59 mL; CLAVICEPS PURPUREA SCLEROTIUM 12 [hp_X]/59 mL; SULFUR 12 [hp_X]/59 mL
INACTIVE INGREDIENTS: WATER; CITRIC ACID MONOHYDRATE; POTASSIUM SORBATE

Grains and Gluten Intolerances™

ACTIVE INGREDIENT

Drug Facts__________________________________________________________________________________________________________

HPUS active ingredients: Arsenicum album, Bryonia, Histaminum hydrochloricum, Hydrastis canadensis, Lycopodium clavatum, Natrum muriaticum, Pulsatilla, Sabadilla, Secale cornutum, Sulphur. Equal volumes of each ingredient in 12X, 24X, LM1 potencies.

INDICATIONS AND USAGE

Uses temporarily relieves symptoms from grains and gluten intolerances and sensitivities: gas, heartburn, headache, nausea, or diarrhea.

Inactive Ingredients:

Bio-Energetically Enhanced™ pure water, citric acid and potassium sorbate.

Warnings

- Stop use and ask your doctor if symptoms persist or worsen.

- If pregnant or breast-feeding, ask a healthcare professional before use.

- Keep out of reach of children

DOSAGE AND ADMINISTRATION

- Initially, depress pump until primed.
- Spray one dose directly into mouth.
- Ages 12 and up- 3 sprays 3 times per day.
- Ages 6-12- 2 sprays 3 times per day.

OTHER SAFETY INFORMATION

Tamper resistant for your protection. Use only if safety seal is intact.

PURPOSE

Uses temporarily relieves symptoms from grains and gluten intolerances and sensitivities:

- gas
- heartburn
- headache
- nausea
- diarrhea